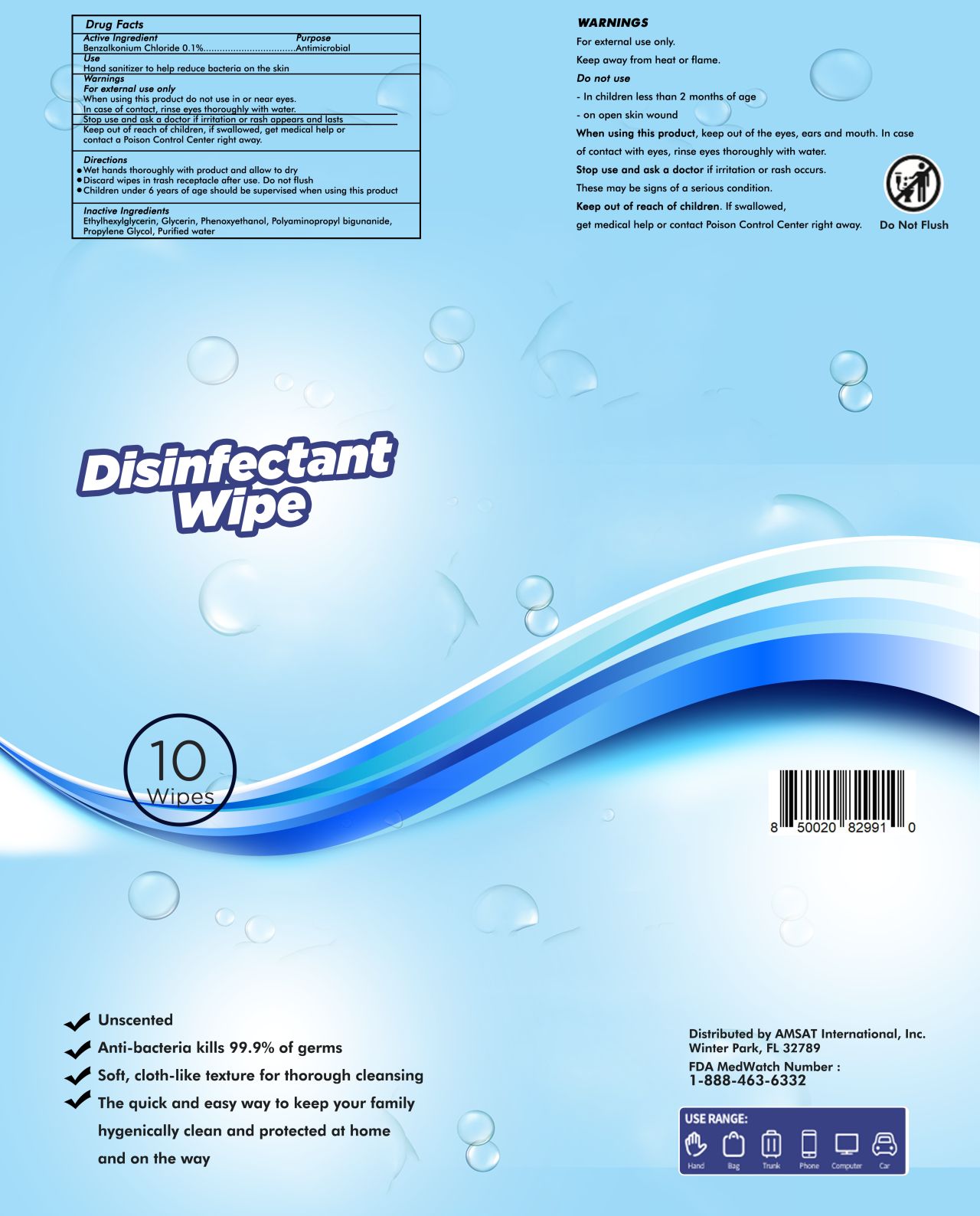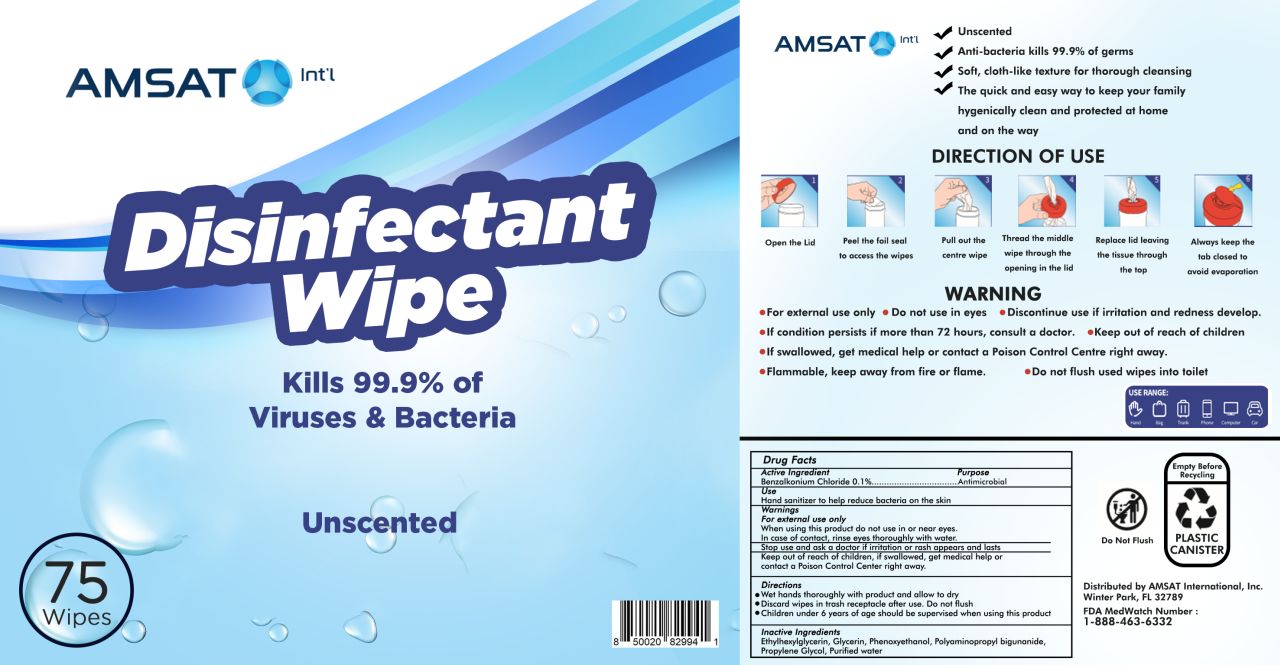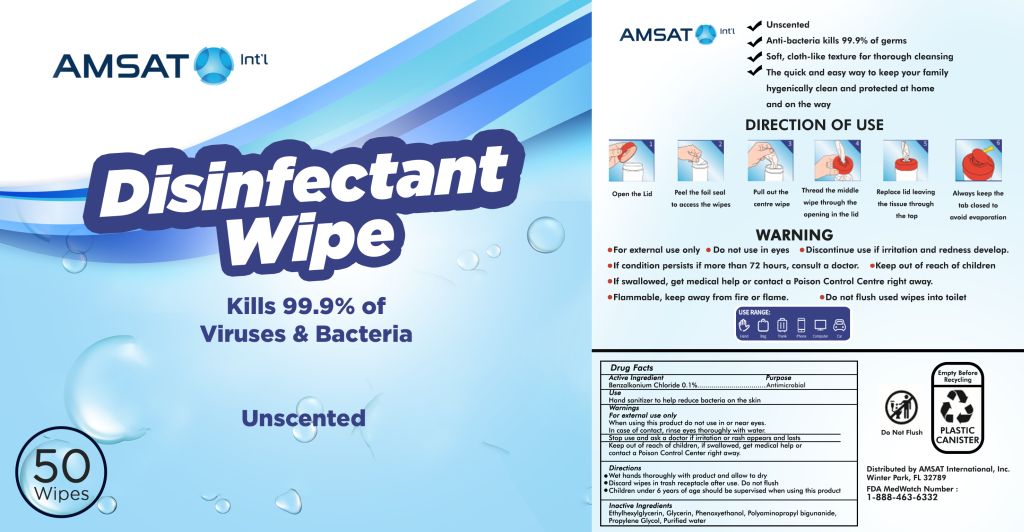 DRUG LABEL: Sanitizer Wipes
NDC: 79438-002 | Form: SOLUTION
Manufacturer: AMSAT International, Inc.
Category: otc | Type: HUMAN OTC DRUG LABEL
Date: 20200818

ACTIVE INGREDIENTS: BENZALKONIUM CHLORIDE 0.1 mg/100 mg
INACTIVE INGREDIENTS: WATER; POLYAMINOPROPYL BIGUANIDE; PROPYLENE GLYCOL; GLYCERIN; PHENOXYETHANOL; ETHYLHEXYLGLYCERIN

Active Ingredient(s)

BENZALKONIUM CHLORIDE 0.1%

Purpose

Purpose: Antimicrobial

Use

Hand Sanitizer to help reduce bacteria on the skin

Warnings

For external use only. Flammable. Keep away from heat or flame

Do not use

- in children less than 2 months of age
- on open skin wounds

When using this product keep out of eyes, ears, and mouth. In case of contact with eyes, rinse eyes thoroughly with water.

Stop use and ask a doctor if irritation or rash occurs. These may be signs of a serious condition.

Keep out of reach of children. If swallowed, get medical help or contact a Poison Control Center right away.

Directions

- Wet hands thoroughly with product and allow to dry.
- Discard wipes in trash receptacle after use. Do not flush
- Children under 6 years of age should be supervised when using this product.

Inactive ingredients

Ethylhexylglycerin, Glycerin, Phenoxyethanol, Polyaminopropyl biguanide, Propylene Glycol, Purified water

Package Label - Principal Display Panel

10 mL NDC: 79438-002-10

75 mL NDC: 79438-002-75

50 mL NDC: 79438-002-50